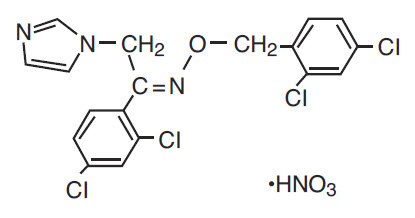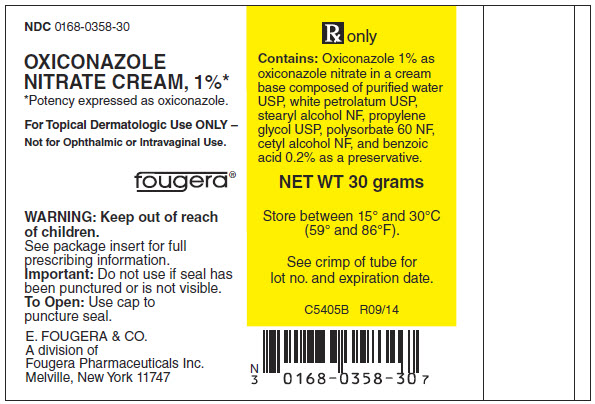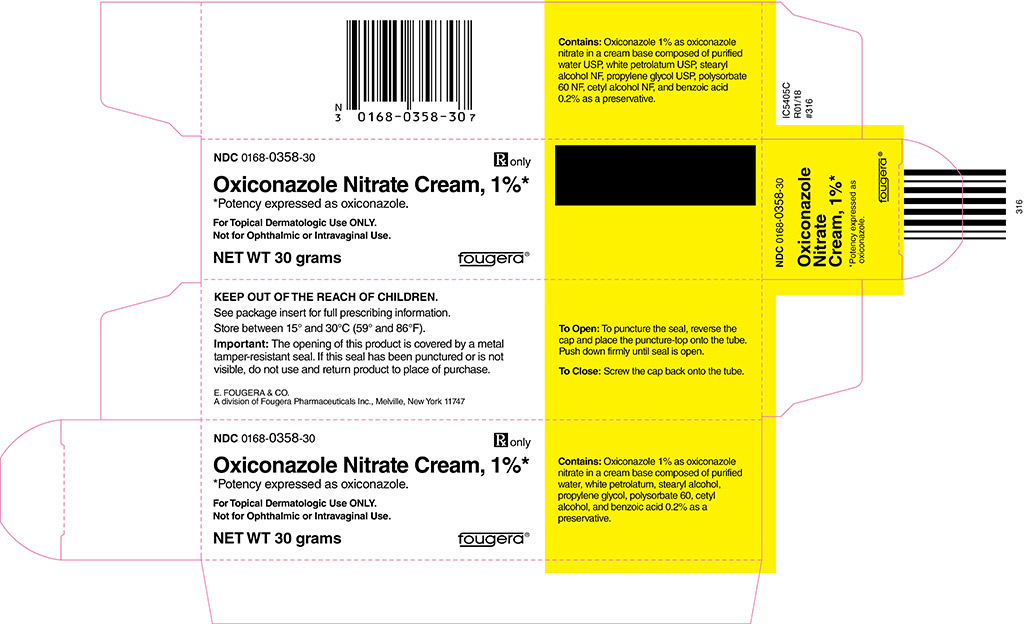 DRUG LABEL: Oxiconazole Nitrate
NDC: 0168-0358 | Form: CREAM
Manufacturer: E. Fougera & Co. a division of Fougera Pharmaceuticals Inc.
Category: prescription | Type: HUMAN PRESCRIPTION DRUG LABEL
Date: 20250708

ACTIVE INGREDIENTS: OXICONAZOLE NITRATE 10 mg/1 g
INACTIVE INGREDIENTS: WATER; PETROLATUM; STEARYL ALCOHOL; PROPYLENE GLYCOL; POLYSORBATE 60; CETYL ALCOHOL; BENZOIC ACID

OXICONAZOLE NITRATE CREAM, 1%*
*Potency expressed as oxiconazole
Rx only
FOR TOPICAL DERMATOLOGIC USE ONLY – NOT FOR OPHTHALMIC OR INTRAVAGINAL USE.

DESCRIPTION

Oxiconazole nitrate cream, 1% contains the antifungal active compound oxiconazole nitrate. This formulation is for topical dermatologic use only.

Chemically, oxiconazole nitrate is 2´,4´-dichloro-2-imidazol-1-ylacetophenone (Z)-[0-(2,4-dichlorobenzyl)oxime], mononitrate. The compound has the molecular formula C18H13ON3CI4•HNO3, a molecular weight of 492.15, and the following structural formula:

Oxiconazole nitrate is a nearly white crystalline powder, soluble in methanol; sparingly soluble in ethanol, chloroform, and acetone; and very slightly soluble in water.

Oxiconazole nitrate cream contains 10 mg of oxiconazole per gram of cream in a white to off-white, opaque cream base of purified water USP, white petrolatum USP, stearyl alcohol NF, propylene glycol USP, polysorbate 60 NF, cetyl alcohol NF, and benzoic acid USP, 0.2% as a preservative.

CLINICAL PHARMACOLOGY

PHARMACOKINETICS

Pharmacokinetics: The penetration of oxiconazole nitrate into different layers of the skin was assessed using an in vitro permeation technique with human skin. Five hours after application of 2.5 mg/cm^2 of oxiconazole nitrate cream onto human skin, the concentration of oxiconazole nitrate was demonstrated to be 16.2 μmol in the epidermis, 3.64 μmol in the upper corium, and 1.29 μmol in the deeper corium. Systemic absorption of oxiconazole nitrate is low. Using radiolabeled drug, less than 0.3% of the applied dose of oxiconazole nitrate was recovered in the urine of volunteer subjects up to 5 days after application of the cream formulation.

Neither in vitro nor in vivo studies have been conducted to establish relative activity between the lotion and cream formulations.

MICROBIOLOGY

Microbiology: Oxiconazole nitrate is an imidazole derivative whose antifungal activity is derived primarily from the inhibition of ergosterol biosynthesis, which is critical for cellular membrane integrity. It has in vitro activity against a wide range of pathogenic fungi.

Oxiconazole has been shown to be active against most strains of the following organisms both in vitro and in clinical infections at indicated body sites (see INDICATIONS AND USAGE):

Epidermophyton floccosum
  Trichophyton mentagrophytes
  Trichophyton rubrum
  Malassezia furfur

The following in vitro data are available; however, their clinical significance is unknown. Oxiconazole exhibits satisfactory in vitro minimum inhibitory concentrations (MICs) against most strains of the following organisms; however, the safety and efficacy of oxiconazole in treating clinical infections due to these organisms have not been established in adequate and well-controlled clinical trials:

Candida albicans
  Microsporum audouini
  Microsporum canis
  Microsporum gypseum
  Trichophyton tonsurans
  Trichophyton violaceum

INDICATIONS AND USAGE

Oxiconazole nitrate cream is indicated for the topical treatment of the following dermal infections: tinea pedis, tinea cruris, and tinea corporis due to Trichophyton rubrum, Trichophyton mentagrophytes, or Epidermophyton floccosum. Oxiconazole nitrate cream is indicated for the topical treatment of tinea (pityriasis) versicolor due to Malassezia furfur (see DOSAGE AND ADMINISTRATION and CLINICAL STUDIES).

Oxiconazole nitrate cream may be used in pediatric patients for tinea corporis, tinea cruris, tinea pedis, and tinea (pityriasis) versicolor; however, these indications for which oxiconazole nitrate cream has been shown to be effective rarely occur in children below the age of 12.

CONTRAINDICATIONS

Oxiconazole nitrate cream is contraindicated in individuals who have shown hypersensitivity to any of their components.

WARNINGS

Oxiconazole nitrate cream, 1% is not for ophthalmic or intravaginal use.

PRECAUTIONS

GENERAL PRECAUTIONS

General: Oxiconazole nitrate cream is for external dermal use only. Avoid introduction of oxiconazole nitrate cream into the eyes or vagina. If a reaction suggesting sensitivity or chemical irritation should occur with the use of oxiconazole nitrate cream, treatment should be discontinued and appropriate therapy instituted. If signs of epidermal irritation should occur, the drug should be discontinued.

PATIENT COUNSELING INFORMATION

Information for Patients: The patient should be instructed to:

1. Use oxiconazole nitrate as directed by the physician. The hands should be washed after applying the medication to the affected area(s). Avoid contact with the eyes, nose, mouth, and other mucous membranes. Oxiconazole nitrate is for external use only.
2. Use the medication for the full treatment time recommended by the physician, even though symptoms may have improved. Notify the physician if there is no improvement after 2 to 4 weeks, or sooner if the condition worsens (see below).
3. Inform the physician if the area of application shows signs of increased irritation, itching, burning, blistering, swelling, or oozing.
4. Avoid the use of occlusive dressings unless otherwise directed by the physician.
5. Do not use this medication for any disorder other than that for which it was prescribed.

DRUG INTERACTIONS

DRUG INTERACTIONS

Drug Interactions: Potential drug interactions between oxiconazole nitrate and other drugs have not been systematically evaluated.

CARCINOGENESIS AND MUTAGENESIS AND IMPAIRMENT OF FERTILITY

Carcinogenesis, Mutagenesis, Impairment of Fertility: Although no long-term studies in animals have been performed to evaluate carcinogenic potential, no evidence of mutagenic effect was found in 2 mutation assays (Ames test and Chinese hamster V79 in vitro cell mutation assay) or in 2 cytogenetic assays (human peripheral blood lymphocyte in vitro chromosome aberration assay and in vivo micronucleus assay in mice).

Reproductive studies revealed no impairment of fertility in rats at oral doses of 3 mg/kg/day in females (1 time the human dose based on mg/m^2) and 15 mg/kg/day in males (4 times the human dose based on mg/m^2). However, at doses above this level, the following effects were observed: a reduction in the fertility parameters of males and females, a reduction in the number of sperm in vaginal smears, extended estrous cycle, and a decrease in mating frequency.

Pregnancy: Teratogenic Effects: Pregnancy Category B.

Reproduction studies have been performed in rabbits, rats, and mice at oral doses up to 100, 150, and 200 mg/kg/day (57, 40, and 27 times the human dose based on mg/m^2), respectively, and revealed no evidence of harm to the fetus due to oxiconazole nitrate. There are, however, no adequate and well-controlled studies in pregnant women. Because animal reproduction studies are not always predictive of human response, this drug should be used during pregnancy only if clearly needed.

NURSING MOTHERS

Nursing Mothers: Because oxiconazole is excreted in human milk, caution should be exercised when the drug is administered to a nursing woman.

PEDIATRIC USE

Pediatric Use: Oxiconazole nitrate cream may be used in pediatric patients for tinea corporis, tinea cruris, tinea pedis, and tinea (pityriasis) versicolor; however, these indications for which oxiconazole nitrate cream has been shown to be effective rarely occur in children below the age of 12.

GERIATRIC USE

Geriatric Use: A limited number of patients at or above 60 years of age (n ~ 396) have been treated with oxiconazole nitrate cream in US and non-US clinical trials. The number of patients is too small to permit separate analysis of efficacy and safety. The adverse reactions reported with oxiconazole nitrate cream in this population were similar to those reported by younger patients. Based on available data, no adjustment of dosage of oxiconazole nitrate cream in geriatric patients is warranted.

ADVERSE REACTIONS

During clinical trials, of 955 patients treated with oxiconazole nitrate cream, 1%, 41 (4.3%) reported adverse reactions thought to be related to drug therapy. These reactions included pruritus (1.6%); burning (1.4%); irritation and allergic contact dermatitis (0.4% each); folliculitis (0.3%); erythema (0.2%); and papules, fissure, maceration, rash, stinging, and nodules (0.1% each).

OVERDOSAGE

When 5% oxiconazole cream (5 times the concentration of the marketed product) was applied at a rate of 1 g/kg to approximately 10% of body surface area of a group of 40 male and female rats for 35 days, 3 deaths and severe dermal inflammation were reported. No overdoses in humans have been reported with use of oxiconazole nitrate cream.

DOSAGE AND ADMINISTRATION

Oxiconazole nitrate cream should be applied to affected and immediately surrounding areas once to twice daily in patients with tinea pedis, tinea corporis, or tinea cruris. Oxiconazole nitrate cream should be applied once daily in the treatment of tinea (pityriasis) versicolor. Tinea corporis, tinea cruris, and tinea (pityriasis) versicolor should be treated for 2 weeks and tinea pedis for 1 month to reduce the possibility of recurrence. If a patient shows no clinical improvement after the treatment period, the diagnosis should be reviewed.

Note: Tinea (pityriasis) versicolor may give rise to hyperpigmented or hypopigmented patches on the trunk that may extend to the neck, arms, and upper thighs. Treatment of the infection may not immediately result in restoration of pigment to the affected sites. Normalization of pigment following successful therapy is variable and may take months, depending on individual skin type and incidental sun exposure. Although tinea (pityriasis) versicolor is not contagious, it may recur because the organism that causes the disease is part of the normal skin flora.

CLINICAL STUDIES

The following definitions were applied to the clinical and microbiological outcomes in patients enrolled in the clinical trials that form the basis for the approval of oxiconazole nitrate cream.

Definitions:

1. Mycological Cure: No evidence (culture and KOH preparation) of the baseline (original) pathogen in a specimen from the affected area taken at the 2-week post-treatment visit (for tinea [pityriasis] versicolor, mycological cure was limited to KOH only).
2. Treatment Success: Both a global evaluation of 90% clinical improvement and a microbiologic eradication (see above) at the 2-week post-treatment visit.

Tinea Pedis: THERE ARE NO HEAD-TO-HEAD COMPAR ISON TRIALS OF THE OXICONAZOLE NITRATE CREAM AND LOTION FORMULATIONS IN THE TREATMENT OF TINEA PEDIS.

The two pivotal trials for the oxiconazole nitrate cream formulation involved 281 evaluable patients (total from both trials) with clinically and microbiologically established tinea pedis.

The combined results of these 2 clinical trials at the 2-week post-treatment follow-up visit are shown in the following table:

Patient Outcome | Oxiconazole Nitrate Cream |  | Vehicle
Patient Outcome | b.i.d. | q.d. | Vehicle
Mycological cure | 77% | 79% | 33%
Treatment success | 52% | 43% | 14%

All the improvement and cure rates of the b.i.d.- and q.d.- treated groups did not differ significantly (95% confidence interval) from each other but were statistically (95% confidence interval) superior to the vehicle-treated group.

In addition, pediatric data (95 children ages 10 and under) available with the cream formulation indicate that it is safe and effective for use in children when used as directed. Adverse events were reported in 2 children; 1 child was reported to have reddening of the skin and 1 child was reported to have eczema-like skin alterations.

Tinea (pityriasis) Versicolor: Two pivotal clinical trials of oxiconazole nitrate cream in tinea (pityriasis) versicolor involved 219 evaluable patients in the q day oxiconazole nitrate and vehicle arms of the trial with clinical and mycological evidence of tinea (pityriasis) versicolor. Patients were treated for 2 weeks with oxiconazole nitrate cream once daily, or with cream vehicle. The combined results of these clinical trials at the 2-week post-treatment follow-up visit are shown in the following table. These results are based on 207 patients (110 in the oxiconazole nitrate group and 97 in the vehicle group) with efficacy evaluations at this visit.

Patient Outcome | Oxiconazole Nitrate Cream | Vehicle
Patient Outcome | q.d. | Vehicle
Mycological cure | 88% | 67%
Treatment success | 83% | 62%

Only once a day was shown in both studies to be statistically superior to vehicle for all efficacy parameters at 2 weeks and follow-up.

HOW SUPPLIED

Oxiconazole nitrate cream, 1% is supplied in:

30 g tubes NDC 0168-0358-30,
  60 g tubes NDC 0168-0358-60,
  90 g tubes NDC 0168-0358-90.

Store between 15° and 30°C (59° and 86°F).

E. FOUGERA & CO.
A division of
Fougera
PHARMACEUTICALS INC.
Melville, New York 11747

46144436A
R09/14
#316

PACKAGE LABEL – PRINCIPAL DISPLAY PANEL – 30 G CONTAINER

NDC 0168-0358-30

OXICONAZOLE
NITRATE CREAM, 1%*
*Potency expressed as oxiconazole.

For Topical Dermatologic Use ONLY -
Not for Ophthalmic or Intravaginal Use.

Rx Only

NET WT 30 grams

PACKAGE LABEL – PRINCIPAL DISPLAY PANEL – 30 G CARTON

NDC 0168-0358-30

Rx Only

OXICONAZOLE NITRATE CREAM, 1%*
*Potency expressed as oxiconazole.

For Topical Dermatologic Use ONLY -
Not for Ophthalmic or Intravaginal Use.

NET WT 30 grams